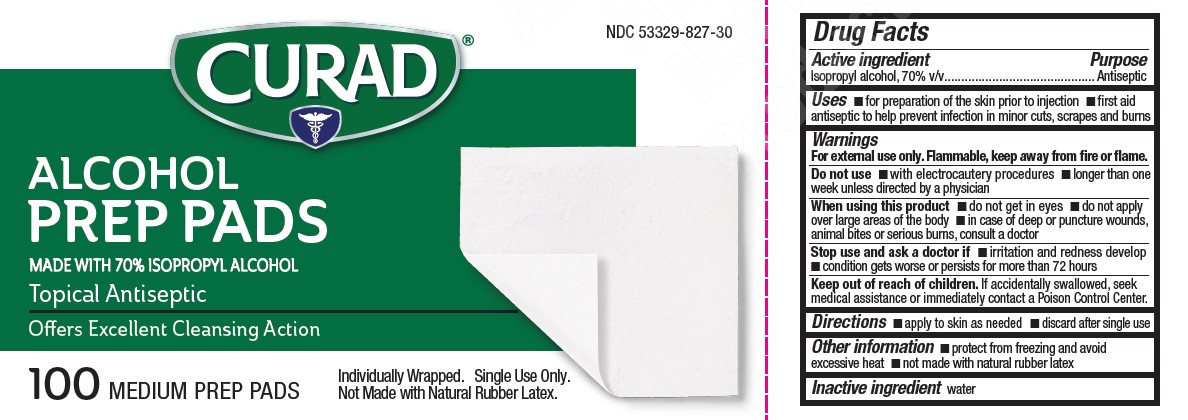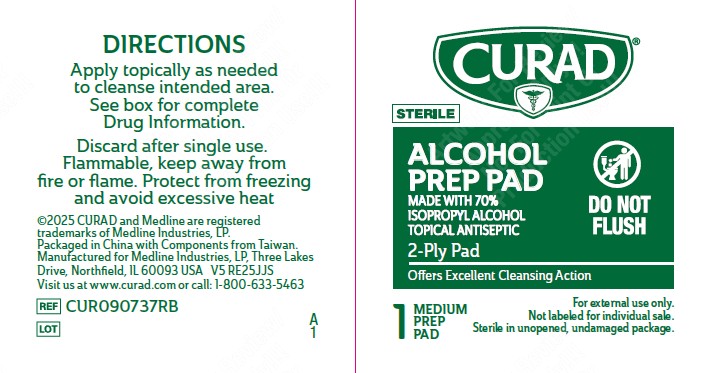 DRUG LABEL: Curad Alcohol Prep Pads
NDC: 53329-827 | Form: SWAB
Manufacturer: Medline Industries, LP
Category: otc | Type: HUMAN OTC DRUG LABEL
Date: 20251015

ACTIVE INGREDIENTS: ISOPROPYL ALCOHOL 70 mL/100 mL
INACTIVE INGREDIENTS: WATER

827 Curad Steril Alcohol Prep Pads

Active ingredient

Isopropyl alcohol, 70% v/v

Purpose

Antiseptic

Uses

- for preparation of the skin prior to injection
- first aid antiseptic to help prevent infection in minor cuts, scrapes and burns

Warnings

For external use only. Flammable, keep away from fire or flame.

Do not use

- with electrocautery procedures
- longer than 1 week unless directed by a physician

When using this product

- do not get into eyes
- do not apply over large areas of the body
- in case of deep or puncture wounds, animal bites or serious burns, consult a doctor

Stop use and ask a doctor if

- irritation and redness develop
- condition gets worse or persists for more than 72 hours

Keep out of reach of children.

If accidentally swallowed, seek medical assistance or immediately contact a Poison Control Center.

Directions

- apply to skin as needed
- discard after single use

Other information

- protect from freezing and avoid excessive heat
- not made with Natural Rubber Latex

Inactive ingredients

water

Manufacturing Information

©2025 CURAD and Medline are registered
trademarks of Medline Industries, LP.
Packaged in China with Components from Taiwan.
Manufactured for Medline Industries, LP, Three Lakes
Drive, Northfield, IL 60093 USA
Visit us at www.curad.com or call: 1-800-633-5463

REF: CUR090737RB